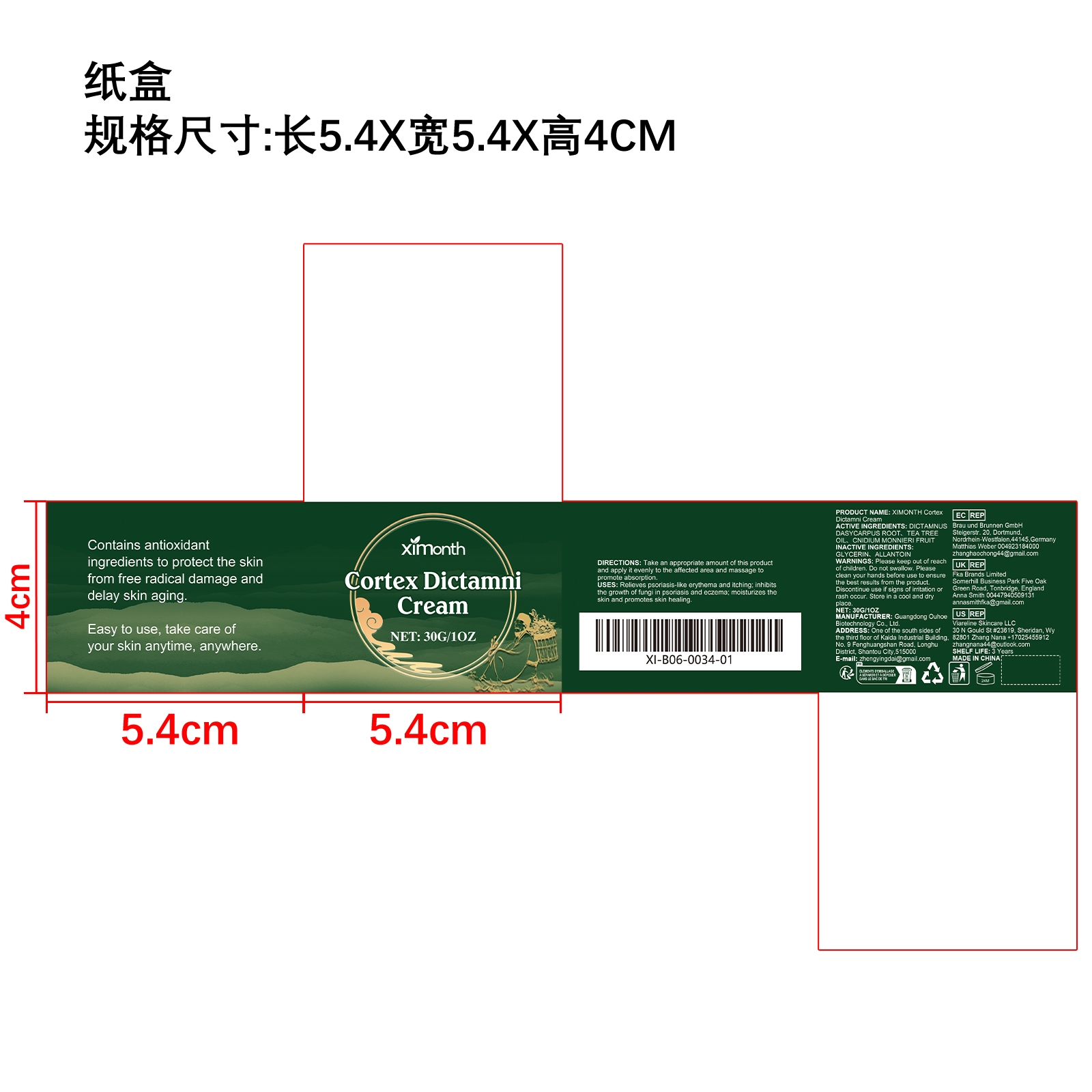 DRUG LABEL: XIMONTH Cortex Dictamni Cream
NDC: 84744-069 | Form: CREAM
Manufacturer: Guangdong Ouhoe Biotechnology Co., Ltd.
Category: otc | Type: HUMAN OTC DRUG LABEL
Date: 20241028

ACTIVE INGREDIENTS: TEA TREE OIL 3 g/30 g; CNIDIUM MONNIERI FRUIT 4.5 g/30 g; DICTAMNUS DASYCARPUS ROOT 9 g/30 g
INACTIVE INGREDIENTS: GLYCERIN 4.5 g/30 g; ALLANTOIN 9 g/30 g

ACTIVE INGREDIENTS

DICTAMNUS DASYCARPUS ROOT， TEA TREE OIL，CNIDIUM MONNIERI FRUIT

PURPOSE

Relieves psoriasis-like erythema and itching; inhibits the growth of fungi in psoriasis andeczema; moisturizes the skin and promotes skin healing.

USE

Take an appropriate amount of this product and apply it evenly to the affected area and massage to promote absorption.

WARNINGS

Please keep out of reach of children. Do not swallow.Please clean your hands before use to ensure the best results from the product. Discontinue use if signs of irritation or rash occur. Store in a cool and dry place.

STOP USE

Discontinue use if signs of irritation or rash occur.

DO NOT USE

Discontinue use if signs of irritation or rash occur.

KEEP OUT OF REACH OF CHILDREN

Please keep out of reach of children. Do not swallow.

STORAGE AND HANDLING

Store in a cool and dry place.

INACTIVE INGREDIENT

GLYCERIN、ALLANTOIN